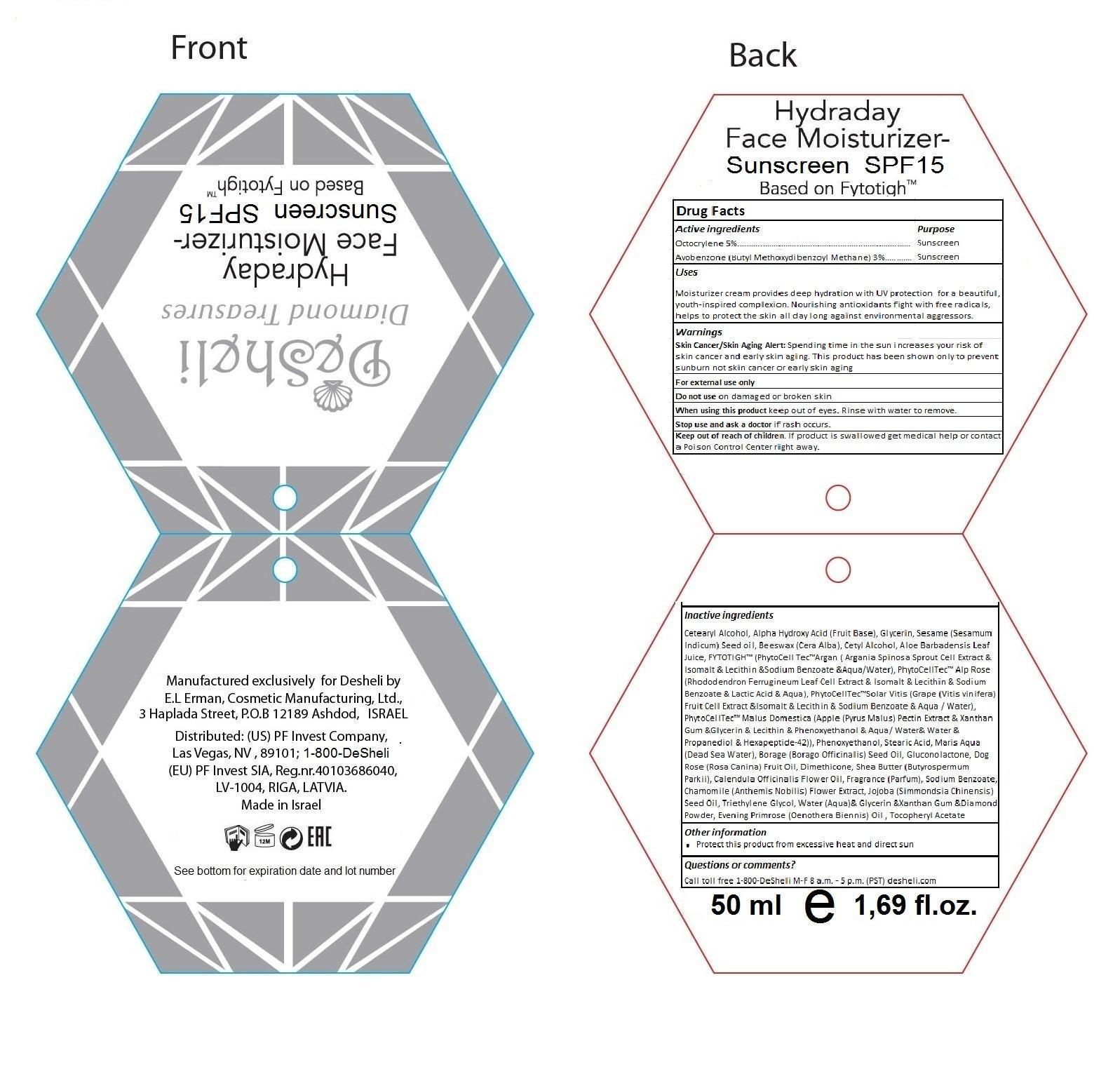 DRUG LABEL: Hydraday
NDC: 61220-001 | Form: CREAM
Manufacturer: PF Invest Company
Category: otc | Type: HUMAN OTC DRUG LABEL
Date: 20131121

ACTIVE INGREDIENTS: OCTOCRYLENE 2.5 mg/50 mg; AVOBENZONE 1.5 mg/50 mg
INACTIVE INGREDIENTS: WATER; CETOSTEARYL ALCOHOL; CITRIC ACID MONOHYDRATE; GLYCERIN; SESAME OIL; YELLOW WAX; CETYL ALCOHOL; ALOE VERA LEAF; ARGANIA SPINOSA WHOLE; ISOMALT; EGG PHOSPHOLIPIDS; SODIUM BENZOATE; MALUS DOMESTICA WHOLE; XANTHAN GUM; PHENOXYETHANOL; STEARIC ACID; BORAGO OFFICINALIS SEED; GLUCONOLACTONE; ROSA CANINA FRUIT OIL; DIMETHICONE; SHEA BUTTER; CALENDULA OFFICINALIS FLOWER; CHAMOMILE FLOWER OIL; JOJOBA OIL; TRIETHYLENE GLYCOL; DIAMOND; EVENING PRIMROSE OIL; TOCOPHEROL

Active Ingredients Purpose

Octocrylene 5% ................................................................. Sunscreen

Avobenzone (Butyl Methoxydibenzoyl Methane) 3% ......... Sunscreen

PURPOSE

Desheli

Diamond Treasure

Hydraday Face Moisturizer - Sunscreen SPF15

Based on Fytotigh™

Manufactured exclusively for Desheli by E.L Erman, Cosmetic Manufacturing, Ltd., 3 Haplada Street, P.O.B 12189 Ashdod, ISRAEL

Distributed: (US) PF Invest Company, Las Vegas, NV, 89101; 1-800-DeSheli (EU) PF Invest SIA, Reg.nr.40103686040, LV-1004, RIGA, LATVIA

Made in Israel

Other Information

Protect this product from excessive heat and direct sun

Questions or comments?

Call toll free 1-800-DeSheli M-F 8 a.m. - 5 p.m. (PST) desheli.com

50 ml e 1,69 fl.oz.

Keep out of reach of children. If product is swallowed get medical help or contact a Poison Control Center right away.

Uses

Moisturizer cream provides deep hydration with UV protection for a beautiful, youth-inspired complexion. Nourishing antioxidants fight with free radicals, helps to protect the skin all day long against environmental aggressors.

Warnings

Skin cancer/skin aging alert: Spending time in the sun increases your risk of skin cancer and early skin aging. This product has been shown only to prevent sunbutn not skin cancer or early skin aging

For external use only

Do not use on damaged or broken skin

When using this product keep out of eyes. Rinse with water to remove.

Stop use and ask a doctor if rash occurs.

Uses

Moisturizer cream provides deep hydration with UV protection for a beautiful, youth-inspired complexion. Nourishing antioxidants fight with free radicals, helps to protect the skin all day long against environmental aggressors.

Inactive Ingredients

Cetearyl alcohol, alpha hydroxy acid (fruit base), glycerin, sesame (sesamum indicum) seed oil, beeswax (cera alba), cetyl alcohol, aloe barbadensis leaf juice, FYTOTIGH™ (PhytoCell Tec™Argan (argania spinosa sprout cell extract & isomalt & lecithin & sodium benzoate & aqua/water), PhytoCell Tec™Solar Vitis (Grape (vitis vinifera) fruit cell extract & isomalt & lecithin & sodium benzoate & aqua/water), PhytoCell Tec™Malus Domestica (apple (pyrus malus) pectin extract & xanthan gum & glycerin & lecithin & phenoxyethanol & aqua/water & propanediol & hexapeptide-42)), phenoxyethanol, stearic acid, maris aqua (Dead Sea water), borage (borago officinalis) seed oil, gluconolactone, dog rose (rosa canina) fruit oil, dimethicone, shea butter (butyrospermum parkii), calendula officinalis flower oil, fragrance (parfum), sodium benzoate, chamomile (anthemis nobilis) flower extract, jojoba (simmondsia chinensis) seed oil, triethylene glycol, water (aqua) & glycerin & xanthan gum & diamond powder, evening primrose (oenothera biennis) oil, tocopheryl acetate